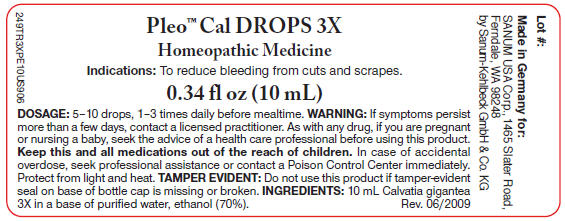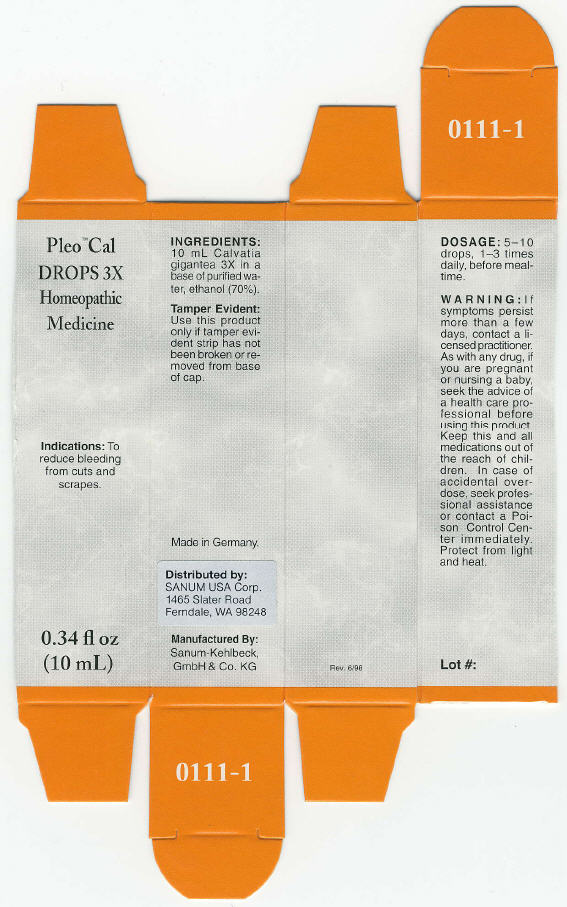 DRUG LABEL: Pleo Cal
NDC: 60681-0111 | Form: SOLUTION/ DROPS
Manufacturer: Sanum Kehlbeck GmbH & Co. KG
Category: homeopathic | Type: HUMAN OTC DRUG LABEL
Date: 20090928

ACTIVE INGREDIENTS: GIANT PUFFBALL 3 [hp_X]/10 mL
INACTIVE INGREDIENTS: water; alcohol

Pleo™ Cal
DROPS 3X

Homeopathic Medicine

Indications

To reduce bleeding from cuts and scrapes.

INGREDIENTS

10 mL Calvatia gigantea 3X in a base of purified water, ethanol (70%).

Tamper Evident

Use this product only if tamper evident strip has not been broken or removed from base of cap.

DOSAGE

5–10 drops, 1–3 times daily, before mealtime.

WARNING

If symptoms persist more than a few days, contact a licensed practitioner. As with any drug, if you are pregnant or nursing a baby, seek the advice of a health care professional before using this product.

KEEP OUT OF REACH OF CHILDREN

Keep this and all medications out of the reach of children. In case of accidental overdose, seek professional assistance or contact a Poison Control Center immediately.

STORAGE AND HANDLING

Protect from light and heat.

Made in Germany.

Distributed by:
SANUM USA Corp.
1465 Slater Road
Ferndale, WA 98248

Manufactured By:
Sanum-Kehlbeck,
GmbH & Co. KG

Rev. 6/98

PRINCIPAL DISPLAY PANEL - 10 mL Label

Pleo™ Cal DROPS 3X

Homeopathic Medicine

Indications: To reduce bleeding from cuts and scrapes.

0.34 fl oz (10 mL)

DOSAGE: 5–10 drops, 1–3 times daily before mealtime. WARNING: If symptoms persist
more than a few days, contact a licensed practitioner. As with any drug, if you are pregnant
or nursing a baby, seek the advice of a health care professional before using this product.
Keep this and all medications out of the reach of children. In case of accidental
overdose, seek professional assistance or contact a Poison Control Center immediately.
Protect from light and heat. TAMPER EVIDENT: Do not use this product if tamper-evident
seal on base of bottle cap is missing or broken. INGREDIENTS: 10 mL Calvatia gigantea
3X in a base of purified water, ethanol (70%).
Rev. 06/2009

PRINCIPAL DISPLAY PANEL - 10 mL Box

Pleo™ Cal
DROPS 3X

Homeopathic
Medicine

Indications: To
reduce bleeding
from cuts and
scrapes.

0.34 fl oz
(10 mL)